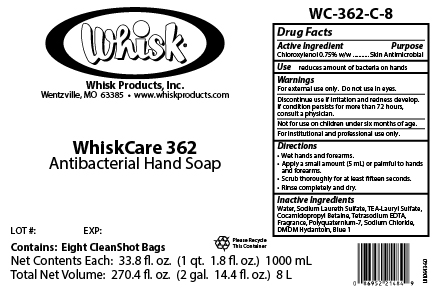 DRUG LABEL: WhiskCare 362
NDC: 65585-562 | Form: SOAP
Manufacturer: Whisk Products, Inc.
Category: otc | Type: HUMAN OTC DRUG LABEL
Date: 20231201

ACTIVE INGREDIENTS: CHLOROXYLENOL 7.5 mg/1 mL
INACTIVE INGREDIENTS: DMDM HYDANTOIN; WATER; TRIETHANOLAMINE LAURYL SULFATE; SODIUM CHLORIDE; FD&C BLUE NO. 1; COCAMIDOPROPYL BETAINE; SODIUM LAURETH SULFATE; EDETATE SODIUM; POLYQUATERNIUM-7 (70/30 ACRYLAMIDE/DADMAC; 1600000 MW)

WhiskCare 362

Active Ingredient

Chloroxylenol 0.75% w/w

Purpose

Skin Antimicrobial

Use

reduces amount of bacteria on hands

Warnings

For external use only. Do not use in eyes.

Discontinue use if irritation and redness develop. If condition persists for more than 72 hours, consult a physician.

KEEP OUT OF REACH OF CHILDREN

Not for use on children under 6 months of age.

For institutional and professional use only.

Directions

- Wet hands and forearms.
- Apply a small amount (5 mL) or palmful to hands and forearms.
- Scrub thoroughly for at least fifteen seconds.
- Rinse completely and dry.

Inactive Ingredients

Water, Sodium Laureth Sulfate, TEA-Lauryl SUlfate, Cocamidopropyl Betaine, Tetrasodium EDTA, Fragrance, Polyquaternium-7, Sodium Chloride, DMDM Hydantoin, Blue 1